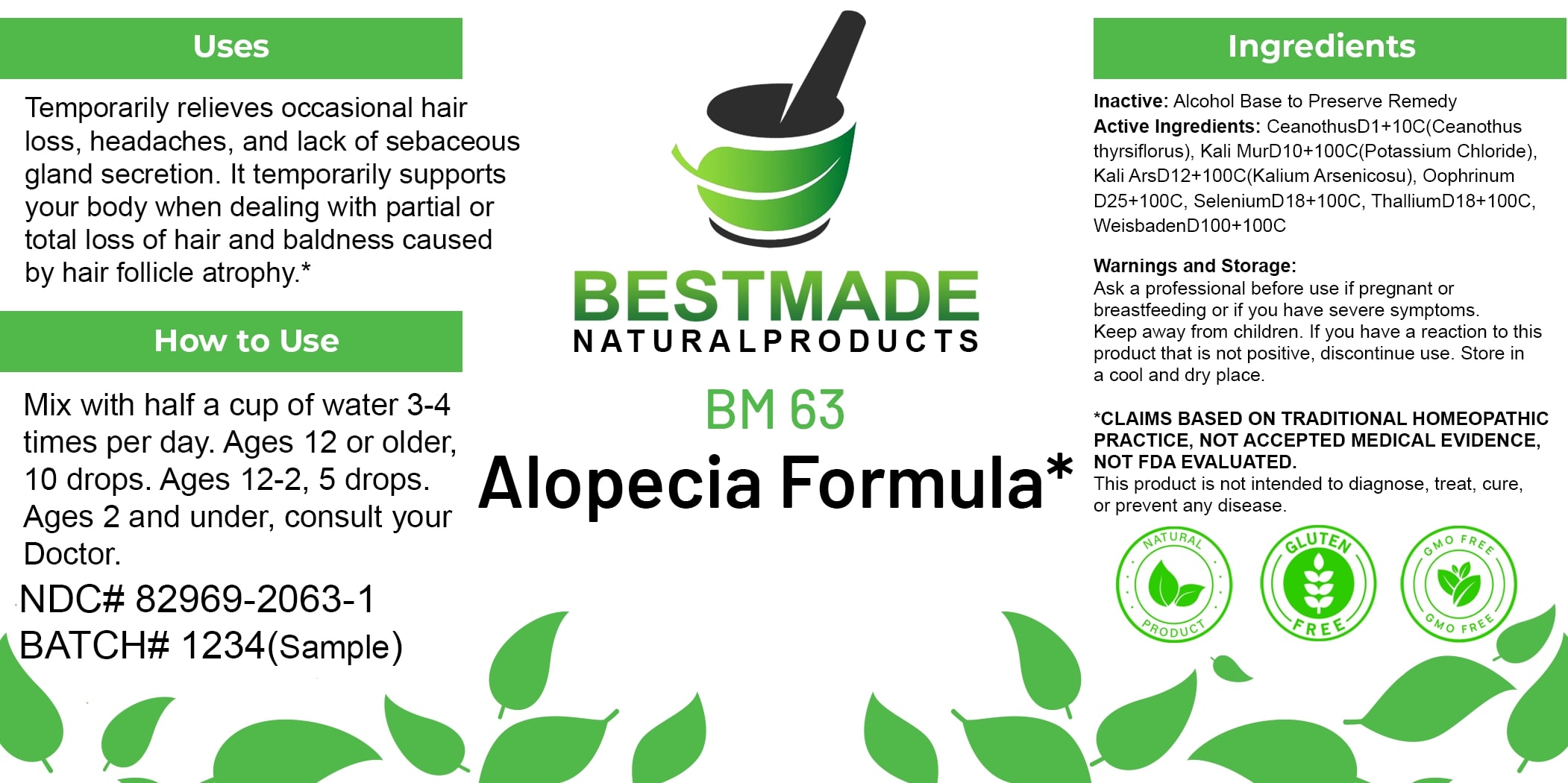 DRUG LABEL: Bestmade Natural Products BM63
NDC: 82969-2063 | Form: LIQUID
Manufacturer: Bestmade Natural Products
Category: homeopathic | Type: HUMAN OTC DRUG LABEL
Date: 20250130

ACTIVE INGREDIENTS: CEANOTHUS THYRSIFLORUS WHOLE 100 [hp_C]/100 [hp_C]; WATER 100 [hp_C]/100 [hp_C]; POTASSIUM CHLORIDE 100 [hp_C]/100 [hp_C]; THALLIUM 100 [hp_C]/100 [hp_C]; SELENIUM 100 [hp_C]/100 [hp_C]; SUS SCROFA OVARY 100 [hp_C]/100 [hp_C]; POTASSIUM ARSENITE ANHYDROUS 100 [hp_C]/100 [hp_C]
INACTIVE INGREDIENTS: ALCOHOL 100 [hp_C]/100 [hp_C]

BM63

DOSAGE AND ADMINISTRATION

How to Use

Mix with half a cup of water 3-4 times per day. Ages 12 or older, 10 drops. Ages 12-2, 5 drops. Ages 2 and under, consult your Doctor.

INACTIVE INGREDIENT

Ingredients

Inactive: Alcohol Base to Preserve Remedy

ACTIVE INGREDIENT

Active Ingredients: CeanothusD1+10C(Ceanothus thyrsiflorus), Kali MurD10+100C(Potassium Chloride), Kali ArsD12+100C(Kalium Arsenicosu), Oophrinum D25+100C, SeleniumD18+100C, ThalliumD18+100C, WeisbadenD100+100C

Uses

Temporarily relieves occasional hair loss, headaches, and lack of sebaceous gland secretion. It temporarily supports your body when dealing with partial or total loss of hair and baldness caused by hair follicle atrophy.*

*CLAIMS BASED ON TRADITIONAL HOMEOPATHIC PRACTICE, NOT ACCEPTED MEDICAL EVIDENCE, NOT FDA EVALUATED.

This product is not intended to diagnose, treat, cure, or prevent any disease.

Uses

Temporarily relieves occasional hair loss, headaches, and lack of sebaceous gland secretion. It temporarily supports your body when dealing with partial or total loss of hair and baldness caused by hair follicle atrophy.*

*CLAIMS BASED ON TRADITIONAL HOMEOPATHIC PRACTICE, NOT ACCEPTED MEDICAL EVIDENCE, NOT FDA EVALUATED.

This product is not intended to diagnose, treat, cure, or prevent any disease.

KEEP OUT OF REACH OF CHILDREN

Warnings and Storage:

Ask a professional before use if pregnant or breastfeeding or if you have severe symptoms. Keep away from children. If you have a reaction to this product that is not positive, discontinue use. Store in a cool and dry place.

Warnings and Storage:

Ask a professional before use if pregnant or breastfeeding or if you have severe symptoms. Keep away from children. If you have a reaction to this product that is not positive, discontinue use. Store in a cool and dry place.

*CLAIMS BASED ON TRADITIONAL HOMEOPATHIC PRACTICE, NOT ACCEPTED MEDICAL EVIDENCE, NOT FDA EVALUATED.

This product is not intended to diagnose, treat, cure, or prevent any disease.

Entire package label